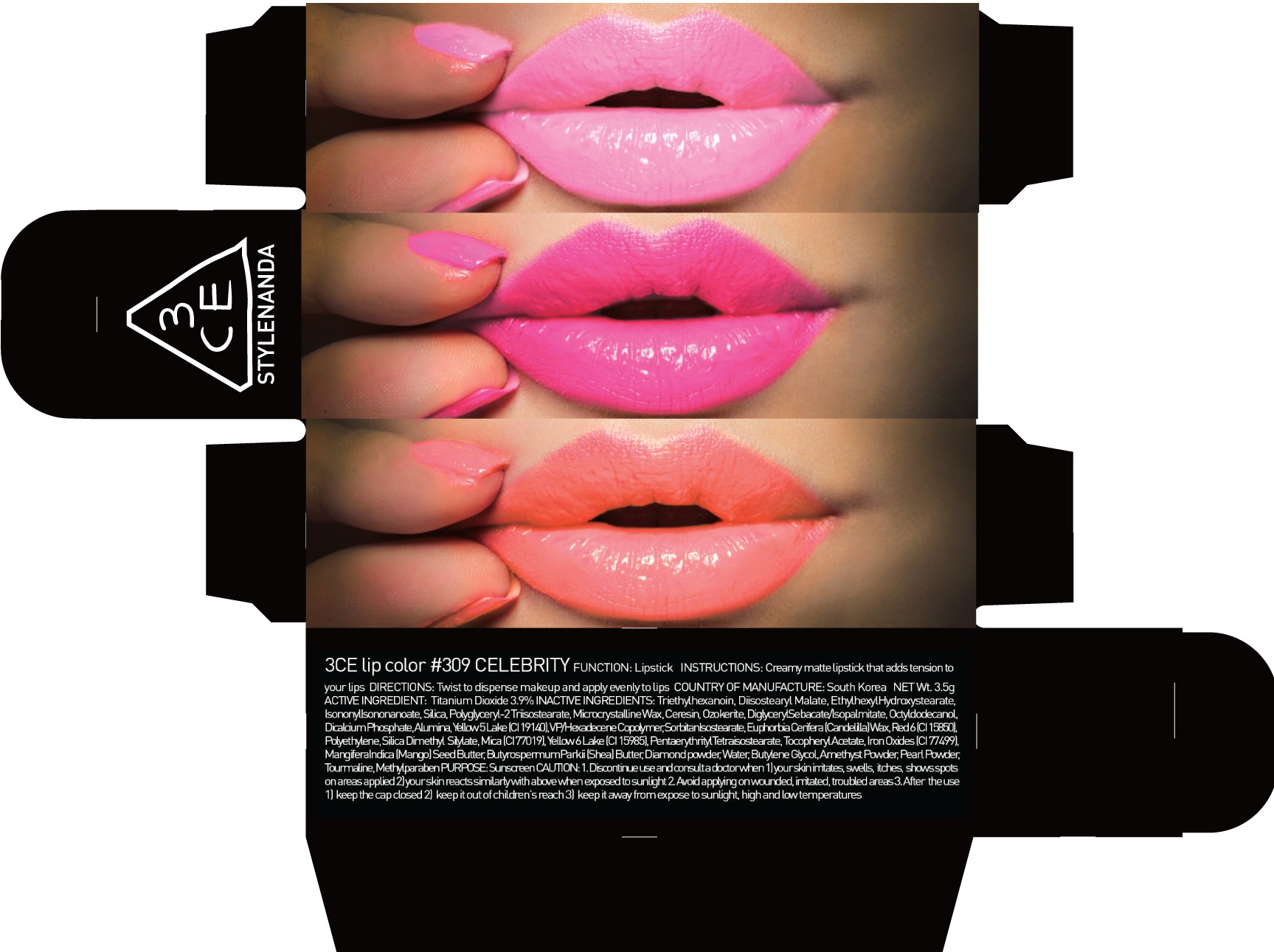 DRUG LABEL: 3CE LIP COLOR 309 CELEBRITY
NDC: 60764-051 | Form: LIPSTICK
Manufacturer: Nanda Co., Ltd
Category: otc | Type: HUMAN OTC DRUG LABEL
Date: 20160930

ACTIVE INGREDIENTS: Titanium Dioxide 0.13 g/3.5 g
INACTIVE INGREDIENTS: Triethylhexanoin; Diisostearyl Malate

ACTIVE INGREDIENT

Active Ingredient: Titanium Dioxide 3.9%

INACTIVE INGREDIENT

Inactive Ingredients: Triethylhexanoin, Diisostearyl Malate, EthylhexylHydroxystearate, IsononylIsononanoate, Silica, Polyglyceryl-2 Triisostearate, Microcrystalline Wax, Ceresin, Ozokerite, DiglycerylSebacate/Isopalmitate, Octyldodecanol, Dicalcium Phosphate, Alumina, Yellow 5 Lake (CI 19140), VP/Hexadecene Copolymer, SorbitanIsostearate, Euphorbia Cerifera (Candelilla) Wax, Red 6 (CI 15850), Polyethylene, Silica Dimethyl Silylate, Mica (CI 77019), Yellow 6 Lake (CI 15985), PentaerythritylTetraisostearate, Tocopheryl Acetate, Iron Oxides (CI 77499), MangiferaIndica (Mango) Seed Butter, ButyrospermumParkii (Shea) Butter, Diamond powder, Water, Butylene Glycol, Amethyst Powder, Pearl Powder, Tourmaline, Methylparaben

PURPOSE

Purpose: Sunscreen

CAUTION

CAUTION: 1. Discontinue use and consult a doctor when - your skin irritates, swells, itches, shows spots on areas applied - your skin reacts similarly with above when exposed to sunlight 2. Avoid applying on wounded, irritated, troubled areas 3. After the use - keep the cap closed - keep it out of children's reach - keep it away from expose to sunlight, high and low temperatures

DESCRIPTION

INSTRUCTIONS: A rich color lipstick that moistly adheres to lips.

Directions: Twist to dispense makeup and apply evenly to lips